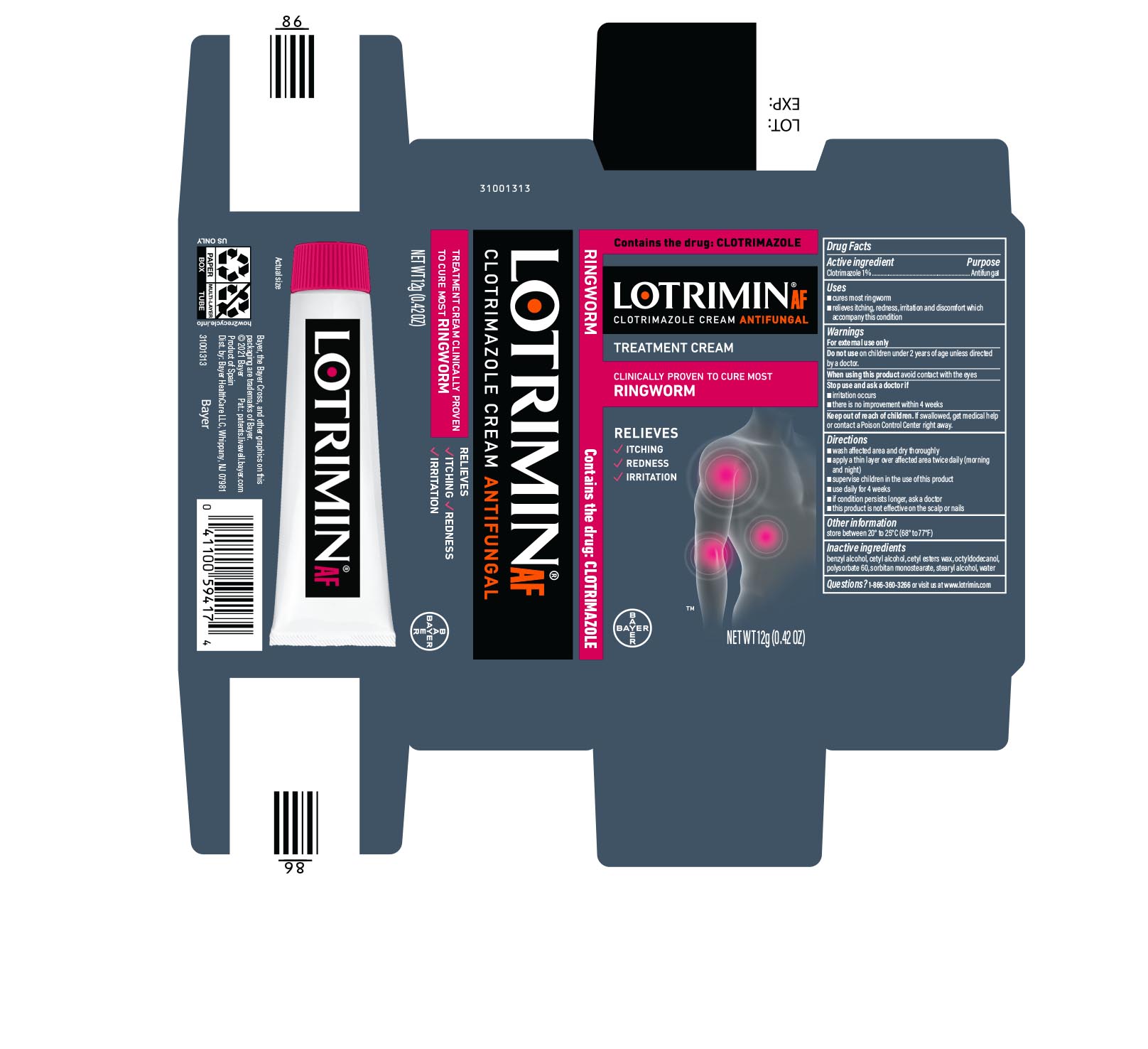 DRUG LABEL: Lotrimin
NDC: 11523-6549 | Form: CREAM
Manufacturer: Bayer HealthCare LLC.
Category: otc | Type: HUMAN OTC DRUG LABEL
Date: 20251205

ACTIVE INGREDIENTS: CLOTRIMAZOLE 10 mg/1 g
INACTIVE INGREDIENTS: CETYL ALCOHOL; BENZYL ALCOHOL; CETYL ESTERS WAX; OCTYLDODECANOL; POLYSORBATE 60; SORBITAN MONOSTEARATE; STEARYL ALCOHOL; WATER

Lotrimin

Drug Facts

Active ingredient

Clotrimazole 1%

Purpose

Antifungal

Uses

- cures most ringworm
- relieves itching, redness, irritation and discomfort which accompany this condition

Warnings

For external use only

When using this product avoid contact with the eyes

Stop use and ask a doctor if

- irritation occurs
- there is no improvement within 4 weeks

Do not use on children under 2 years of age unless directed by a doctor.

Keep out of reach of children. If swallowed, get medical help or contact a Poison Control Center right away.

Directions

- wash affected area and dry thoroughly
- apply a thin layer over affected area twice daily (morning and night)
- supervise children in the use of this product
- use daily for 4 weeks
- if condition persists longer, ask a doctor
- this product is not effective on the scalp or nails

Other information

store between 20° to 25°C (68° to 77°F)

Inactive ingredients

benzyl alcohol, cetyl alcohol, cetyl esters wax, octyldodecanol, polysorbate 60, sorbitan monostearate, stearyl alcohol, water

Questions?

1-866-360-3266

Distributed by Bayer HealthCare LLC, Whippany, NJ, USA, 07981

PRINCIPAL DISPLAY PANEL - 12 g Tube Carton

LOTRIMIN® AF
ANTIFUNGAL
clotrimazole cream

NET WT 12g (0.42 OZ)